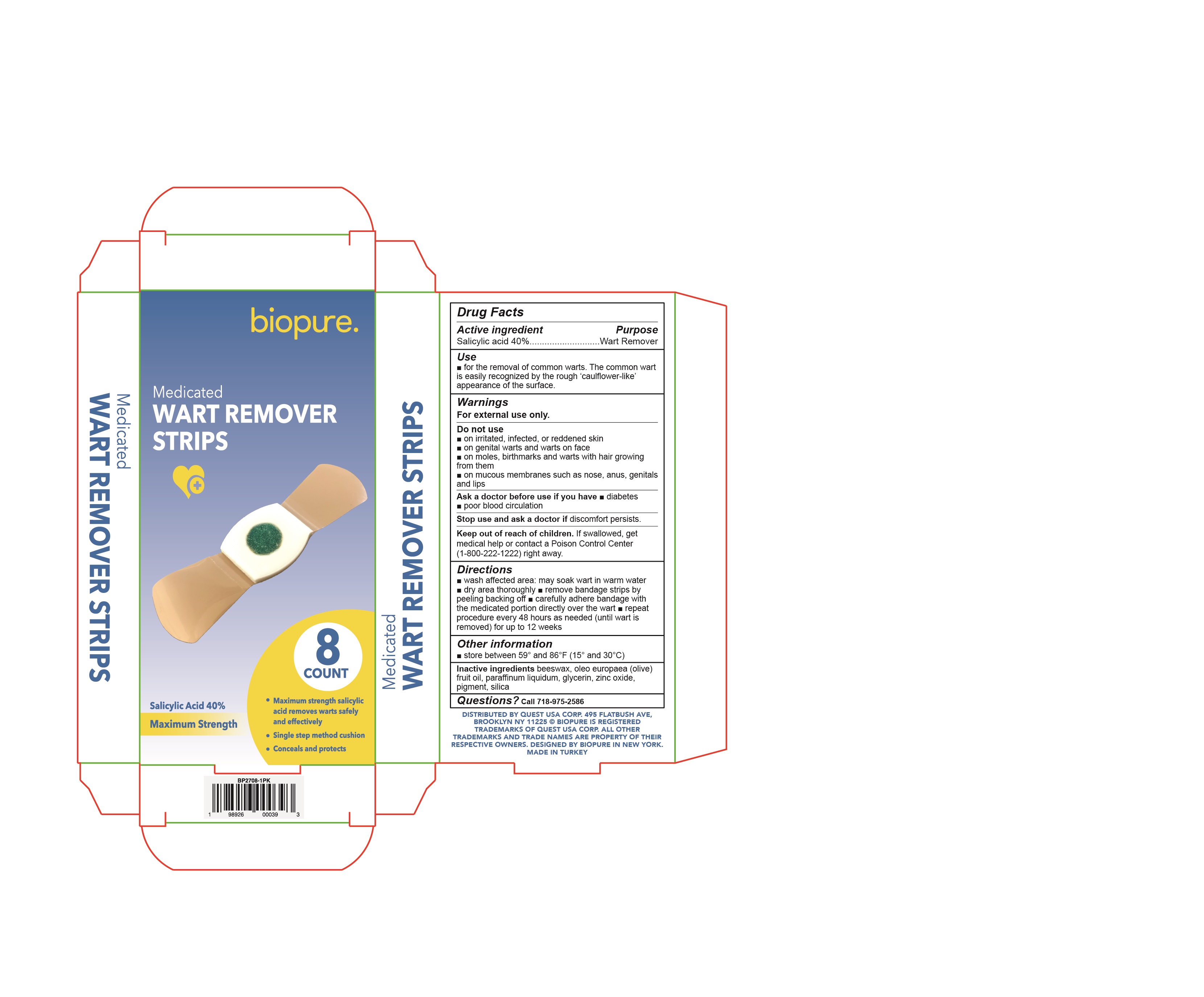 DRUG LABEL: Biopure Medicated Wart Remover Strips
NDC: 78691-308 | Form: PLASTER
Manufacturer: QUEST USA CORP
Category: otc | Type: HUMAN OTC DRUG LABEL
Date: 20250307

ACTIVE INGREDIENTS: SALICYLIC ACID 0.4 g/1 g
INACTIVE INGREDIENTS: GLYCERIN; ZINC OXIDE; OLIVE OIL; FD&C BLUE NO. 1; SILICON DIOXIDE; MINERAL OIL; YELLOW WAX; FD&C YELLOW NO. 5; TITANIUM DIOXIDE

Biopure Medicated Wart Remover Strips

Active ingredient

Salicylic Acid 40%

Purpose

Wart Remover

Uses

- for the removal of common plantar warts. The common wart is easily recognized by the rough "cauliflower-like" appearance of the surface.

Warnings

For external use only.

Stop use and ask a doctor if

discomfort persists.

Do not use

•on irritated skin or on any area that is infected or reddened skin

•genital warts, or warts on the face

•on moles, birthmarks, warts with hair growing from them

• mucous membranes such as nose, anus, genitals and lips

Keep out of reach of children.If swallowed, get medical help or contact a Poison Control Center (1-800-222-1222) right away.

Directions

- wash affected area: may soak wart in warm water for 5 minutes
- dry area thoroughly
- peel off backing paper
- adhere medicated patch directly over wart
- repeat this procedure every 48 hours as needed (until wart is removed) for up to 12 weeks

Other information

store between 59º and 86°F (15º and 30ºC)

Questions?

please call 1-718-975-2586

Inactive Ingridients

beeswax, oleo europaea (olive) fruit oil, paraffinum liquidum, glycerin, zinc oxide, pigment, silica